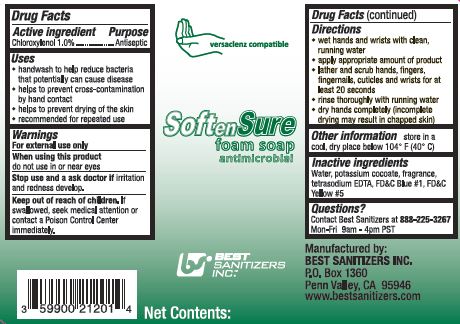 DRUG LABEL: SoftenSure Foam Antimicrobial
NDC: 59900-127 | Form: LIQUID
Manufacturer: Best Sanitizers, Inc.
Category: otc | Type: HUMAN OTC DRUG LABEL
Date: 20241205

ACTIVE INGREDIENTS: CHLOROXYLENOL 10 mg/1 mL
INACTIVE INGREDIENTS: WATER; POTASSIUM COCOATE; EDETATE SODIUM; FD&C BLUE NO. 1; FD&C YELLOW NO. 5

Drug Facts 5900-127

Active ingredient

Chloroxylenol 1.0%

Purpose

Antiseptic

Uses

- handwash to help reduce bacteria that potentially can cause disease

- helps to prevent cross-contamination by hand contact

- helps to prevent drying of the skin

- recommended for repeated use

Warnings

For external use only

When using this product

do not use in or near eyes

Stop use and ask a doctor ifirritation and redness develop.

Keep out of reach of children.

If swallowed, seek medical attention or contact a Poison Control Center immediately.

Directions

- wet hands and wrists with clean, running water

- apply appropriate amount of product

- lather and scrub hands, fingers, fingernails, cuticles and wrists for at least 20 seconds

- rinse thoroughly with running water

- dry hands completely (incomplete drying may result in chapped skin)

Other information

store in a cool, dry place below 104oF (40oC)

Inactive ingredients

Water, potassium cocoate, fragrance, tetrasodium EDTA, FDC Blue 1, FDC Yellow 5

Questions?

Contact Best Sanitizers at 888-225-3267 Mon-Fri 9am - 4pm PST

PACKAGE LABEL

versaclenz compatible

SoftenSure

foam soap

antimicrobial

BEST

SANITIZERS

INC.

Net Contents: